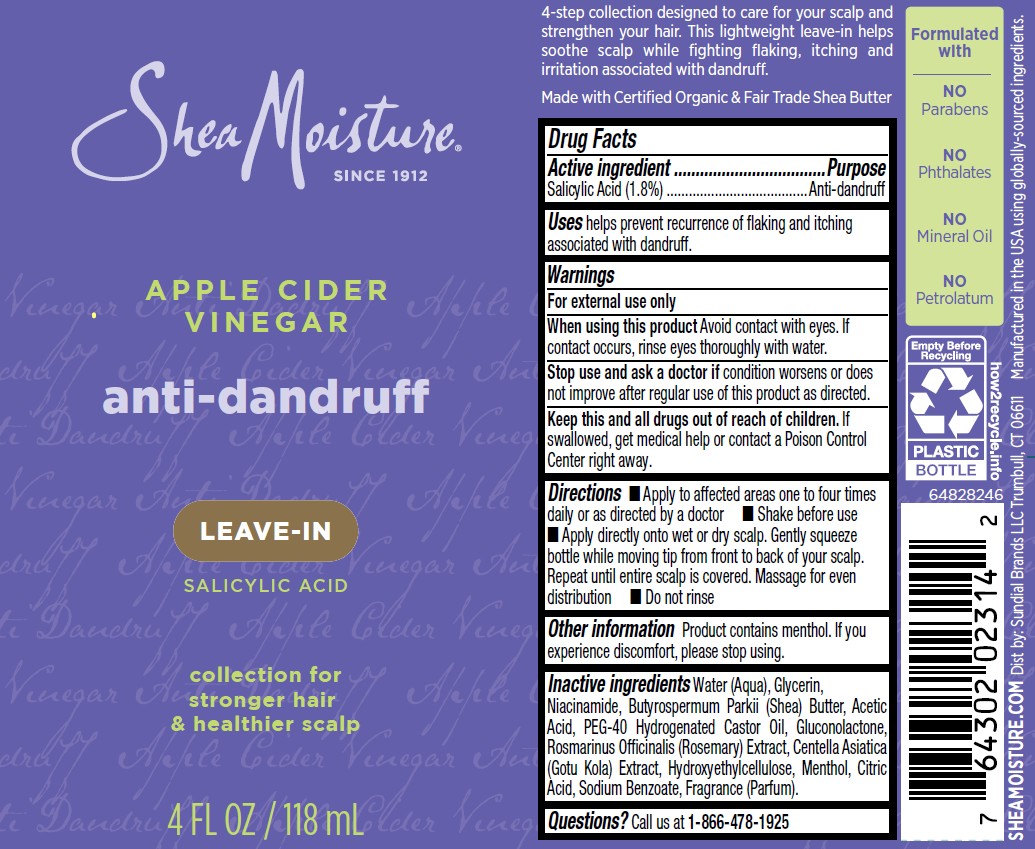 DRUG LABEL: Shea Moisture
NDC: 64942-2391 | Form: LIQUID
Manufacturer: Conopco, Inc. d/b/a Unilever
Category: otc | Type: HUMAN OTC DRUG LABEL
Date: 20251016

ACTIVE INGREDIENTS: SALICYLIC ACID 1.8 g/100 mL
INACTIVE INGREDIENTS: MENTHOL; CITRIC ACID; WATER; ACETIC ACID; BUTYROSPERMUM PARKII (SHEA) BUTTER; CENTELLA ASIATICA; SODIUM BENZOATE; HYDROXYETHYLCELLULOSE; PEG-40 HYDROGENATED CASTOR OIL; GLUCONOLACTONE; ROSEMARY; NIACINAMIDE; GLYCERIN

Shea Moisture Apple Cider Vinegar Anti-dandruff Leave-in

DESCRIPTION

Shea Moisture Apple Cider Vinegar Anti-dandruff Leave-in

ACTIVE INGREDIENT

Salicylic acid (1.8%)

PURPOSE

Anti-dandruff

INDICATIONS AND USAGE

Uses helps prevent recurrence of flaking and itching associated with dandruff.

WARNINGS

For external use only. When using this product Avoid contact with eyes. If contact occurs, rinse eyes thoroughly with water. Stop use and ask a doctor if condition worsens or does not improve after regular use of this product as directed..

KEEP OUT OF REACH OF CHILDREN

Keep this and all drugs out of reach of children. If swallowed, get medical help or contact a Poison Control Center right away.

DOSAGE AND ADMINISTRATION

■ Apply to affected areas one to four times daily or as directed by a doctor ■ Shake before use ■ Apply directly onto wet or dry scalp. Gently squeeze bottle while moving tip from front to back of your scalp. Repeat until entire scalp is covered. Massage for even distribution ■ Do not rinse

OTHER SAFETY INFORMATION

Product contains menthol. If you experience discomfort, please stop using.

INACTIVE INGREDIENT

Water (Aqua), Glycerin, Niacinamide, Butyrospermum Parkii (Shea) Butter, Acetic Acid, PEG-40 Hydrogenated Castor Oil, Gluconolactone, Rosmarinus Officinalis (Rosemary) Extract, Centella Asiatica (Gotu Kola) Extract, Hydroxyethylcellulose, Menthol, Citric Acid, Sodium Benzoate, Fragrance (Parfum)

QUESTIONS

Call us at 1-866-478-1925